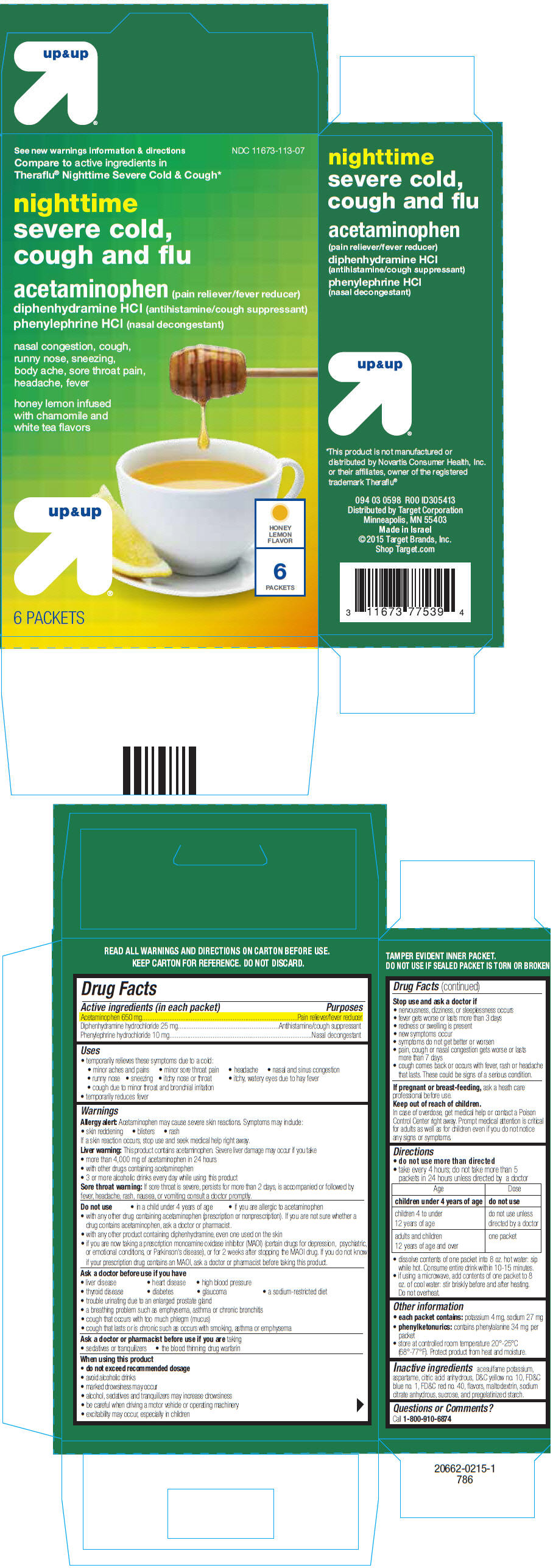 DRUG LABEL: up and up

NDC: 11673-113 | Form: POWDER, FOR SOLUTION
Manufacturer: Target Corporation
Category: otc | Type: HUMAN OTC DRUG LABEL
Date: 20250715

ACTIVE INGREDIENTS: ACETAMINOPHEN 650 mg/1 1; DIPHENHYDRAMINE HYDROCHLORIDE 25 mg/1 1; PHENYLEPHRINE HYDROCHLORIDE 10 mg/1 1
INACTIVE INGREDIENTS: ACESULFAME POTASSIUM; ASPARTAME; ANHYDROUS CITRIC ACID; D&C YELLOW NO. 10; FD&C BLUE NO. 1; FD&C RED NO. 40; MALTODEXTRIN; ANHYDROUS TRISODIUM CITRATE; SUCROSE

up & up
nighttime flu and severe cold and cough

Drug Facts

ACTIVE INGREDIENT

PURPOSE

Active ingredients (in each packet) | Purposes
Acetaminophen 650 mg | Pain reliever/fever reducer
Diphenhydramine hydrochloride 25 mg | Antihistamine/cough suppressant
Phenylephrine hydrochloride 10 mg | Nasal decongestant

Uses

- temporarily relieves these symptoms due to a cold:
  - minor aches and pains
  - minor sore throat pain
  - headache
  - nasal and sinus congestion
  - runny nose
  - sneezing
  - itchy nose or throat
  - itchy, watery eyes due to hay fever
  - cough due to minor throat and bronchial irritation
- temporarily reduces fever

Warnings

Allergy alert

Acetaminophen may cause severe skin reactions. Symptoms may include:

- skin reddening
- blisters
- rash

If a skin reaction occurs, stop use and seek medical help right away.

Liver warning

This product contains acetaminophen. Severe liver damage may occur if you take

- more than 4,000 mg of acetaminophen in 24 hours
- with other drugs containing acetaminophen
- 3 or more alcoholic drinks every day while using this product

Sore throat warning

If sore throat is severe, persists for more than 2 days, is accompanied or followed by fever, headache, rash, nausea, or vomiting consult a doctor promptly.

Do not use

- in a child under 4 years of age
- if you are allergic to acetaminophen
- with any other drug containing acetaminophen (prescription or nonprescription). If you are not sure whether a drug contains acetaminophen, ask a doctor or pharmacist.
- with any other product containing diphenhydramine, even one used on the skin
- if you are now taking a prescription monoamine oxidase inhibitor (MAOI) (certain drugs for depression, psychiatric, or emotional conditions, or Parkinson's disease), or for 2 weeks after stopping the MAOI drug. If you do not know if your prescription drug contains an MAOI, ask a doctor or pharmacist before taking this product.

Ask a doctor before use if you have

- liver disease
- heart disease
- high blood pressure
- thyroid disease
- diabetes
- glaucoma
- a sodium-restricted diet
- trouble urinating due to an enlarged prostate gland
- a breathing problem such as emphysema, asthma or chronic bronchitis
- cough that occurs with too much phlegm (mucus)
- cough that lasts or is chronic such as occurs with smoking, asthma or emphysema

Ask a doctor or pharmacist before use if you aretaking

- sedatives or tranquilizers
- the blood thinning drug warfarin

When using this product

- do not exceed recommended dosage
- avoid alcoholic drinks
- marked drowsiness may occur
- alcohol, sedatives and tranquilizers may increase drowsiness
- be careful when driving a motor vehicle or operating machinery
- excitability may occur, especially in children

Stop use and ask a doctor if

- nervousness, dizziness, or sleeplessness occurs
- fever gets worse or lasts more than 3 days
- redness or swelling is present
- new symptoms occur
- symptoms do not get better or worsen
- pain, cough or nasal congestion gets worse or lasts more than 7 days
- cough comes back or occurs with fever, rash or headache that lasts. These could be signs of a serious condition.

PREGNANCY OR BREAST FEEDING

If pregnant or breast-feeding,ask a heath care professional before use.

Keep out of reach of children.

In case of overdose, get medical help or contact a Poison Control Center right away. Prompt medical attention is critical for adults as well as for children even if you do not notice any signs or symptoms.

Directions

- do not use more than directed
- take every 4 hours; do not take more than 5 packets in 24 hours unless directed by a doctor

Age | Dose
children under 4 years of age | do not use
children 4 to under 12 years of age | do not use unless directed by a doctor
adults and children 12 years of age and over | one packet

- dissolve contents of one packet into 8 oz. hot water: sip while hot. Consume entire drink within 10-15 minutes.
- if using a microwave, add contents of one packet to 8 oz. of cool water: stir briskly before and after heating. Do not overheat.

Other information

- each packet contains:potassium 4 mg, sodium 27 mg
- phenylketonurics:contains phenylalanine 34 mg per packet
- store at controlled room temperature 20°-25°C (68°-77°F). Protect product from heat and moisture.

Inactive ingredients

acesulfame potassium, aspartame, citric acid anhydrous, D&C yellow no. 10, FD&C blue no. 1, FD&C red no. 40, flavors, maltodextrin, sodium citrate anhydrous, sucrose, and pregelatinized starch.

Questions or Comments?

Call 1-800-910-6874

Distributed by Target Corporation
Minneapolis, MN 55403

PRINCIPAL DISPLAY PANEL - 6 Packet Carton

See new warnings information & directions

NDC 11673-113-07

Compare toactive ingredients in
Theraflu® Nighttime Severe Cold & Cough*

nighttime
severe cold,
cough and flu

acetaminophen (pain reliever/fever reducer)
diphenhydramine HCl (antihistamine/cough suppressant)
phenylephrine HCl (nasal decongestant)

nasal congestion, cough,
runny nose, sneezing,
body ache, sore throat pain,
headache, fever

honey lemon infused
with chamomile and
white tea flavors

up & up

HONEY
LEMON
FLAVOR

6
PACKETS

6 PACKETS